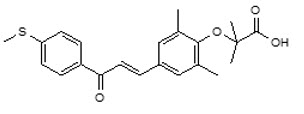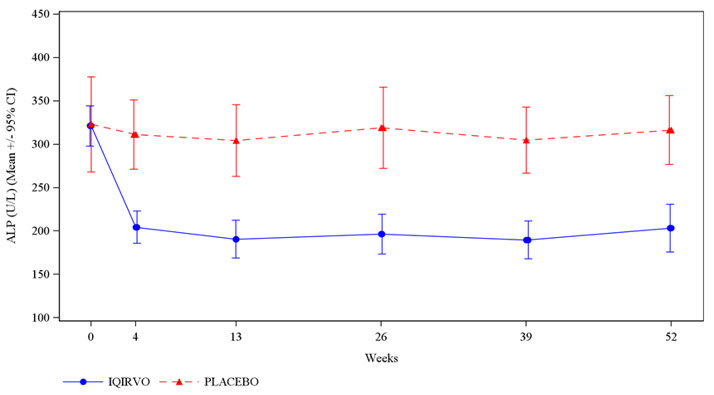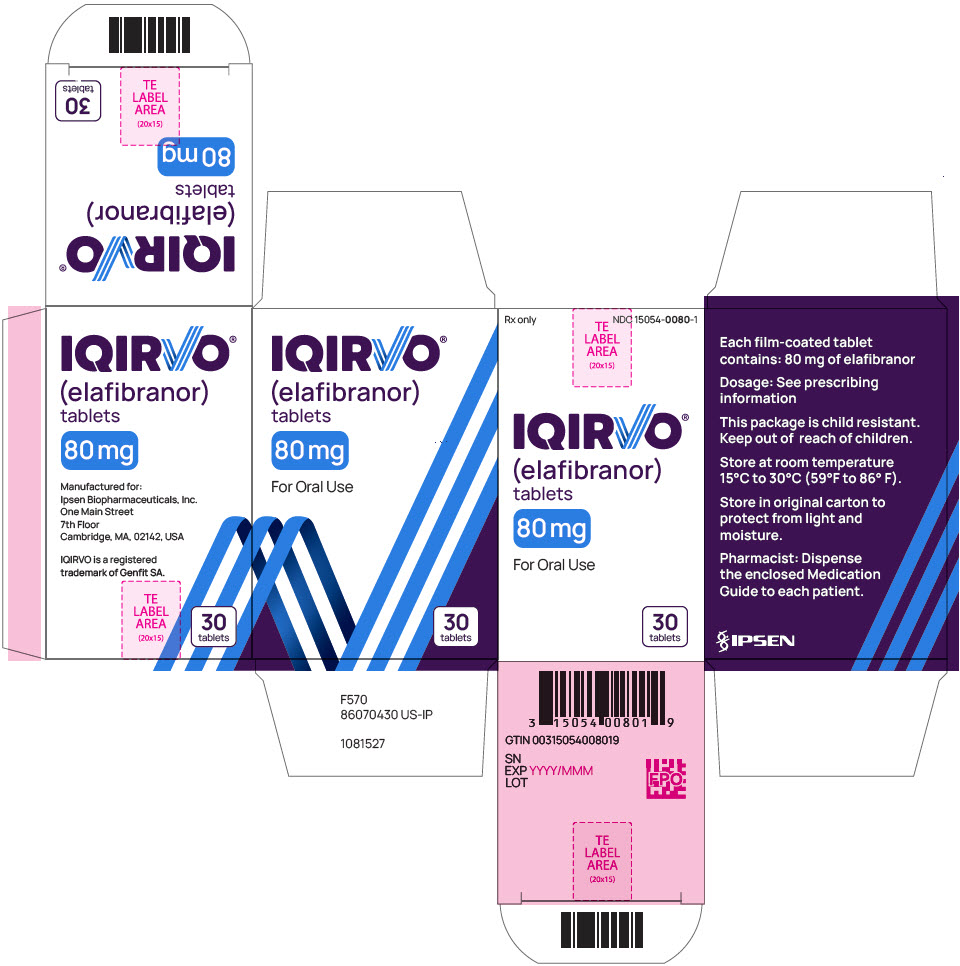 DRUG LABEL: IQIRVO
NDC: 15054-0080 | Form: TABLET, FILM COATED
Manufacturer: Ipsen Biopharmaceuticals, Inc.
Category: prescription | Type: HUMAN PRESCRIPTION DRUG LABEL
Date: 20240610

ACTIVE INGREDIENTS: elafibranor 80 mg/1 1
INACTIVE INGREDIENTS: Microcrystalline cellulose; POVIDONE, UNSPECIFIED; Croscarmellose Sodium; Magnesium Stearate; SILICON DIOXIDE; POLYVINYL ALCOHOL, UNSPECIFIED; Titanium dioxide; POLYETHYLENE GLYCOL 3350; Talc; FERRIC OXIDE YELLOW; FERRIC OXIDE RED

HIGHLIGHTS OF PRESCRIBING INFORMATION

These highlights do not include all the information needed to use IQIRVO® safely and effectively. See full prescribing information for IQIRVO.
IQIRVO (elafibranor) tablets, for oral use
Initial U.S. Approval: 2024

1 INDICATIONS AND USAGE

IQIRVO is a peroxisome proliferator-activated receptor (PPAR) agonist indicated for the treatment of primary biliary cholangitis (PBC) in combination with ursodeoxycholic acid (UDCA) in adults who have an inadequate response to UDCA, or as monotherapy in patients unable to tolerate UDCA.

This indication is approved under accelerated approval based on reduction of alkaline phosphatase (ALP). Improvement in survival or prevention of liver decompensation events have not been demonstrated. Continued approval for this indication may be contingent upon verification and description of clinical benefit in confirmatory trial(s). (1)

Limitations of Use

Use of IQIRVO is not recommended in patients who have or develop decompensated cirrhosis (e.g., ascites, variceal bleeding, hepatic encephalopathy). (8.7, 12.3)

2 DOSAGE AND ADMINISTRATION

- Before treatment, evaluate for muscle pain or myopathy, and/or verify that females of reproductive potential are not pregnant. (2.1)
- The recommended dosage is 80 mg orally once daily with or without food. (2.2)

3 DOSAGE FORMS AND STRENGTHS

Tablets: 80 mg (3)

4 CONTRAINDICATIONS

None.

5 WARNINGS AND PRECAUTIONS

- Myalgia, Myopathy, and Rhabdomyolysis: Assess for muscle pain and myopathy prior to IQIRVO initiation. Consider periodic assessment (clinical exam, CPK measurement). Interrupt IQIRVO if there is new onset or worsening of muscle injury, or muscle pain. (5.1)
- Fractures: The risk of fracture should be considered in the care of patients treated with IQIRVO. Apply current standards of care for assessing and maintaining bone health. (5.2)
- Adverse Effects on Fetal and Newborn Development: May cause fetal harm. Verify that a female of reproductive potential is not pregnant prior to initiating IQIRVO. Advise females of reproductive potential of the potential risk to a fetus and to use effective contraception. (5.3, 8.1, 8.3)
- Drug-Induced Liver Injury: Obtain clinical and laboratory assessments at treatment initiation and monitor thereafter according to routine patient management. Interrupt the treatment if liver tests worsen, or patients develop signs and symptoms consistent with clinical hepatitis. Consider permanent discontinuation if liver tests worsen after restarting IQIRVO. (5.4)
- Hypersensitivity Reactions: If severe hypersensitivity reactions occur, permanently discontinue IQIRVO. If a mild or moderate hypersensitivity reaction occurs, interrupt IQIRVO and treat promptly. Monitor until signs and symptoms resolve. (5.5)
- Biliary Obstruction: Avoid use in patients with complete biliary obstruction. If biliary obstruction is suspected, interrupt IQIRVO and treat as clinically indicated. (5.6)

6 ADVERSE REACTIONS

Most common adverse reactions with IQIRVO (reported in ≥ 5% and higher compared to placebo) are weight gain, diarrhea, abdominal pain, nausea, vomiting, arthralgia, constipation, muscle injury, fracture, gastroesophageal reflux disease, dry mouth, weight loss, and rash. (6.1)

To report SUSPECTED ADVERSE REACTIONS, contact Ipsen Biopharmaceuticals, Inc. at 1-855-463-5127 or FDA at 1-800-FDA-1088 or www.fda.gov/medwatch.

7 DRUG INTERACTIONS

- Hormonal Contraceptives: Switch to effective non-hormonal contraceptives or add a barrier method when using hormonal contraceptives and for at least 3 weeks after last dose. (7.1)
- HMG-CoA Reductase Inhibitors: Monitor for signs and symptoms of muscle injury. (5.1, 7.1)
- Rifampin: Monitor the biochemical response (e.g., ALP and bilirubin) when patients initiate rifampin during IQIRVO treatment. (7.2)
- Bile Acid Sequestrants: Administer at least 4 hours before or 4 hours after taking a bile acid binding sequestrant, or at as great an interval as possible. (2.3, 7.2)

8 USE IN SPECIFIC POPULATIONS

- Lactation: Advise not to breastfeed during treatment and for 3 weeks after last dose. (8.2)
- Hepatic Impairment: Monitor patients with cirrhosis for evidence of decompensation. Consider discontinuation if patient progresses to moderate or severe hepatic impairment (Child-Pugh B or C). (8.7)

FULL PRESCRIBING INFORMATION

1 INDICATIONS AND USAGE

IQIRVO is indicated for the treatment of primary biliary cholangitis (PBC) in combination with ursodeoxycholic acid (UDCA) in adults who have had an inadequate response to UDCA, or as monotherapy in patients unable to tolerate UDCA.

This indication is approved under accelerated approval based on reduction of alkaline phosphatase (ALP) [see Clinical Studies (14)]. Improvement in survival or prevention of liver decompensation events have not been demonstrated. Continued approval for this indication may be contingent upon verification and description of clinical benefit in confirmatory trial(s).

Limitations of Use

Use of IQIRVO is not recommended in patients who have or develop decompensated cirrhosis (e.g., ascites, variceal bleeding, hepatic encephalopathy) [see Use in Specific Populations (8.7), Clinical Pharmacology (12.3)].

2 DOSAGE AND ADMINISTRATION

2.1 Recommended Evaluation Before Initiating IQIRVO

Before initiating IQIRVO:

- Evaluate for muscle pain or myopathy [see Warnings and Precautions (5.1)].
- Verify that females of reproductive potential are not pregnant prior to initiating treatment with IQIRVO [see Warnings and Precautions (5.3), Use in Specific Populations (8.1, 8.3)].

2.2 Recommended Dosage and Administration

The recommended dosage of IQIRVO is 80 mg taken orally once daily with or without food [see Clinical Pharmacology (12.3)].

2.3 Administration Modification for Bile Acid Sequestrants

Administer IQIRVO at least 4 hours before or 4 hours after administering the bile acid sequestrant, or at as great an interval as possible [see Drug Interactions (7.2)].

3 DOSAGE FORMS AND STRENGTHS

Tablets: 80 mg, round, orange, film-coated tablets, debossed with "ELA 80" on one side and plain on the other side.

4 CONTRAINDICATIONS

None.

5 WARNINGS AND PRECAUTIONS

5.1 Myalgia, Myopathy, and Rhabdomyolysis

Rhabdomyolysis resulting in acute kidney injury occurred in one IQIRVO-treated patient who had cirrhosis at baseline and was also taking a stable dose of an HMG-CoA reductase inhibitor (statin). Myalgia or myopathy, with or without CPK elevations, occurred in patients treated with IQIRVO alone or treated concomitantly with a stable dose of an HMG-CoA reductase inhibitor [see Adverse Reactions (6.1)].

Assess for myalgia and myopathy prior to IQIRVO initiation. Consider periodic assessment (clinical exam, CPK measurement) during treatment with IQIRVO, especially in those who have signs and symptoms of new onset or worsening of muscle pain or myopathy. Interrupt IQIRVO treatment if there is new onset or worsening of muscle pain, or myopathy, or rhabdomyolysis.

5.2 Fractures

Fractures occurred in 6% of IQIRVO-treated patients compared to no placebo-treated patients [see Adverse Reactions (6.1)].

Consider the risk of fracture in the care of patients treated with IQIRVO and monitor bone health according to current standards of care.

5.3 Adverse Effects on Fetal and Newborn Development

Based on findings from animal reproduction studies, IQIRVO may cause fetal harm when administered during pregnancy. Treatment of pregnant rats with elafibranor at maternal plasma drug exposures lower than or approximately equal to human exposure at the recommended dose resulted in stillbirths, reduced survival, decrease in pup body weight, and/or blue/black discoloration of the caudal section of body.

For females of reproductive potential, verify that the patient is not pregnant prior to initiation of therapy. Advise females of reproductive potential to use effective non-hormonal contraceptives or add a barrier method when using hormonal contraceptives during treatment with IQIRVO and for 3 weeks following the last dose of IQIRVO [see Drug Interactions (7.1), Use in Specific Populations (8.1, 8.3)].

5.4 Drug-Induced Liver Injury

Drug-induced liver injury (DILI) occurred in one patient who took IQIRVO 80 mg once daily [see Adverse Reactions (6.1)] and two patients who took IQIRVO at 1.5-times the recommended dosage. In one patient who developed DILI while taking IQIRVO at 1.5-times the recommended dosage, the clinical presentation was drug-induced autoimmune-like hepatitis (DI-ALH). The median time to onset of elevation in liver tests was 85 days (range: day 57 to 288). In Study 1, increases in transaminases (alanine aminotransferase [ALT] and aspartate aminotransferase [AST] ≥ 5× ULN) occurred in 6% of IQIRVO-treated patients compared to 6% of placebo-treated patients, and total bilirubin (TB) elevation (> 3× ULN) occurred in 2% of IQIRVO-treated patients compared to no placebo-treated patients.

Obtain baseline clinical and laboratory assessments at treatment initiation with IQIRVO and monitor thereafter according to routine patient management. Interrupt IQIRVO treatment if liver tests (ALT, AST, TB, and/or alkaline phosphatase [ALP]) worsen, or the patient develops signs and symptoms consistent with clinical hepatitis (e.g., jaundice, right upper quadrant pain, eosinophilia). Consider permanent discontinuation if liver tests worsen after restarting IQIRVO.

5.5 Hypersensitivity Reactions

Hypersensitivity reactions have occurred in a clinical trial with IQIRVO at 1.5-times the recommended dosage. Three patients (0.2%) had rash or unspecified allergic reaction that occurred 2 to 30 days after IQIRVO initiation, with positive dechallenges and rechallenges. Hypersensitivity reactions resolved after discontinuation of IQIRVO and treatment with steroids and/or antihistamines.

If a severe hypersensitivity reaction occurs, permanently discontinue IQIRVO. If a mild or moderate hypersensitivity reaction occurs, interrupt IQIRVO and treat promptly. Monitor the patient until signs and symptoms resolve. If a hypersensitivity reaction recurs after IQIRVO rechallenge, then permanently discontinue IQIRVO.

5.6 Biliary Obstruction

Avoid use of IQIRVO in patients with complete biliary obstruction. If biliary obstruction is suspected, interrupt IQIRVO and treat as clinically indicated [see Adverse Reactions (6.1)].

6 ADVERSE REACTIONS

The following clinically significant adverse reactions are described elsewhere in the labeling:

- Myalgia, Myopathy, and Rhabdomyolysis [see Warnings and Precautions (5.1)]
- Fractures [see Warnings and Precautions (5.2)]
- Drug-Induced Liver Injury [see Warnings and Precautions (5.4)]
- Hypersensitivity Reactions [see Warnings and Precautions (5.5)]

6.1 Clinical Trials Experience

Because clinical trials are conducted under widely varying conditions, adverse reaction rates observed in the clinical trials of a drug cannot be directly compared to rates in the clinical trials of another drug and may not reflect the rates observed in practice.

The safety of IQIRVO is based on Study 1 consisting of 161 patients who were randomized to receive IQIRVO 80 mg (n=108) or placebo (n=53) once daily with a median duration of exposure during the double-blind period of 62 weeks (inter quartile range: 52, 84) [see Clinical Studies (14)]. IQIRVO or placebo was administered in combination with UDCA in 95% of patients and as monotherapy in 5% of patients who were unable to tolerate UDCA.

The most common adverse reaction leading to treatment discontinuation was increased CPK (4%).

Common Adverse Reactions

Table 1 presents common adverse reactions that occurred in Study 1.

Table 1: Common Adverse Reactions Occurring During the Double-Blind Period in Adult Patients with PBC (Study 1) [Included 8 patients (5%) who were intolerant to UDCA and initiated treatment as monotherapy: 6 patients (5%) in the IQIRVO arm and 2 patients (4%) in the placebo arm.]
Adverse Reaction [Occurring in greater than or equal to 5% of patients in the IQIRVO treatment arm and at an incidence greater than or equal to 1% higher than in the placebo treatment arm.] | IQIRVO 80 mg Once Daily N = 108 % (n) | Placebo N = 53 % (n)
Weight gain [Weight gain, abdominal pain, muscle pain, fracture, and rash include other related terms.] | 23% (25) | 21% (11)
Diarrhea | 11% (12) | 9% (5)
Abdominal pain | 11% (12) | 6% (3)
Nausea | 11% (12) | 6% (3)
Vomiting | 11% (12) | 2% (1)
Arthralgia | 8% (9) | 4% (2)
Constipation | 8% (9) | 2% (1)
Muscle pain | 7% (8) | 2% (1)
Fracture | 6% (7) | 0
Gastroesophageal reflux disease | 6% (7) | 2% (1)
Dry mouth | 5% (5) | 2% (1)
Weight loss | 5% (5) | 0
Rash | 5% (5) | 4% (2)

Myalgia, Myopathy, and Rhabdomyolysis

Muscle injury included rhabdomyolysis, CPK elevation with or without myalgia, and myopathy. Rhabdomyolysis and acute kidney injury (AKI) occurred in one IQIRVO-treated patient who had cirrhosis at baseline and was also on a stable dose of an HMG-CoA reductase inhibitor for a year. Median time to development of myalgia was 85.5 days (interquartile range: 29, 291). CPK elevation and/or myalgia occurred in patients on IQIRVO monotherapy as well as in patients who were concomitantly treated with an HMG-CoA reductase inhibitor.

Table 2 presents the frequency of muscle injury related adverse reactions in Study 1.

Table 2: Muscle Injury Related Adverse Reactions During the Double-Blind Period in Adult Patients with PBC in Study 1
Adverse Reaction | IQIRVO 80 mg Once Daily N = 108 % (n) | Placebo N = 53 % (n)
Creatine phosphokinase (CPK) increased (>3× ULN) | 4% (4) [Two patients receiving IQIRVO 80 mg once daily were on a concomitant HMG-CoA reductase inhibitor] | 0
Myalgia | 4% (4) | 2% (1)
CPK increased and Myalgia | 1% (1) [One patient receiving IQIRVO 80 mg once daily was on a concomitant HMG-CoA reductase inhibitor] | 0
Rhabdomyolysis and AKI [AKI: Acute kidney injury] | 1% (1) | 0

Fractures

Fractures occurred in 6% (n=7) of IQIRVO-treated patients compared to no placebo-treated patients. The median time to fracture after receiving IQIRVO was 122 days (interquartile range: 48, 258).

Less Common Adverse Reactions

Additional adverse reactions that occurred more frequently in the IQIRVO-treated patients compared to placebo, but in less 5% of patients included dizziness, gastroenteritis, increased blood creatinine, and anemia.

Cholelithiasis and Cholecystitis

New onset of cholelithiasis was detected in 3 (3%) IQIRVO-treated patients compared to no placebo-treated patients. The three IQIRVO-treated patients were taking UDCA concomitantly. An additional patient who had gallstones at baseline developed cholecystitis requiring cholecystectomy.

7 DRUG INTERACTIONS

7.1 Effects of IQIRVO on Other Drugs

Table 3 includes clinically significant drug interactions affecting other drugs.

Table 3: Clinically Significant Interactions Affecting Other Drugs
Hormonal Contraceptives
Clinical Impact | IQIRVO is a weak CYP3A4 inducer [see Clinical Pharmacology (12.3)]. Co-administration of IQIRVO and hormonal contraceptives (e.g., birth control pills, skin patches, implant) may reduce the systemic exposure of progestin and ethinyl estradiol (CYP3A4 substrates), which may lead to contraceptive failure and/or an increase in breakthrough bleeding.
Intervention | Switch to effective non-hormonal contraceptives or add a barrier method when using hormonal contraceptives during treatment with IQIRVO and for at least 3 weeks after last dose [see Warnings and Precautions (5.3), Use in Specific Populations (8.1, 8.3)].
HMG-CoA Reductase Inhibitors
Clinical Impact | CPK elevation and/or myalgia occurred in patients on IQIRVO monotherapy. Co-administration of IQIRVO and HMG-CoA reductase inhibitors (statins) which have a risk of myalgia, can increase the risk of myopathy by a mechanism that has not been fully characterized [see Adverse Reactions (6.1)].
Intervention | Monitor for signs and symptoms of muscle injury. Consider periodic assessment (clinical exam, CPK) during treatment. Interrupt IQIRVO treatment if there is new onset or worsening of muscle pain or myopathy [see Warnings and Precautions (5.1)].

7.2 Effects of Other Drugs on IQIRVO

Table 4 includes clinically significant drug interactions affecting IQIRVO.

Table 4: Clinically Significant Interactions Affecting IQIRVO
Rifampin
Clinical Impact | Co-administration of IQIRVO with rifampin, an inducer of metabolizing enzymes, may reduce the systemic exposure of elafibranor and its active metabolite via increased metabolism and may result in delayed or suboptimal biochemical response [see Clinical Pharmacology (12.3)].
Intervention | Monitor the biochemical response (e.g., ALP and bilirubin) when patients initiate rifampin during treatment with IQIRVO.
Bile Acid Binding Sequestrants
Clinical Impact | Bile acid sequestrants may interfere with the action of IQIRVO by reducing its absorption and systemic exposure, which may reduce IQIRVO efficacy.
Intervention | Administer IQIRVO at least 4 hours before or 4 hours after taking a bile acid binding sequestrant, or at as great an interval as possible [see Dosage and Administration (2.3)].

8 USE IN SPECIFIC POPULATIONS

8.1 Pregnancy

Risk Summary

Based on data from animal reproduction studies, IQIRVO may cause fetal harm when administered during pregnancy. Treatment of pregnant rats with elafibranor during organogenesis through lactation resulted in stillbirths, reduced survival, decrease in pup body weight, and/or blue/black discoloration of the caudal section of body, which occurred at maternal plasma drug exposures lower than or approximately equal to human exposure at the recommended dose (see Data). There are insufficient data from human pregnancies exposed to IQIRVO to allow an assessment of a drug-associated risk of major birth defects, miscarriage, or other adverse maternal or fetal outcomes.

The background risk of major birth defects and miscarriage for the indicated population is unknown. All pregnancies have a background risk of birth defect, loss, or other adverse outcomes. In the U.S. general population, the estimated background risk of major birth defects and miscarriage in clinically recognized pregnancies is 2-4% and 15-20%, respectively.

Report pregnancies to Ipsen Pharmaceuticals, Inc. Adverse Event reporting line at 1-855-463-5127 and [https://www.ipsen.com/contact-us/].

Data

Animal Data

No effects on embryo-fetal development were observed in pregnant rats treated orally with up to 300 mg/kg/day elafibranor (15-times the recommended dose based on combined AUC [area under the plasma concentration-time curve] for elafibranor and GFT1007) during the period of organogenesis.

No adverse effects on embryo-fetal development were observed in pregnant rabbits treated orally with doses up to 100 mg/kg/day elafibranor, which produced systemic exposures (combined AUC for elafibranor and GFT1007) during the period of organogenesis that were less than the human exposure. Administration of 300 mg/kg/day (3.9-times the recommended dose based on combined AUC for elafibranor and GFT1007) produced marked maternal toxicity, embryo-lethality, reduced fetal weight, and a low incidence of fetal malformations. Variations in ossification of distal limb bones occurred at 100 mg/kg/day, which was associated with strong signs of maternal toxicity (e.g., body weight loss).

A pre- and postnatal development study was performed using oral administration of 10, 30, or 100 mg/kg/day elafibranor in female rats during organogenesis through lactation. All doses produced a reduction in pup survival (during postnatal days 1-4 at 100 mg/kg/day and postnatal days 5-21 at 10 mg/kg/day and higher), a decrease in pup body weight (dose-dependent, up to -28% on postnatal day 1), blue/black discoloration of the caudal section of body, and developmental delays based on evaluation of physical landmarks and functional tests. The developmental delays were likely caused by the decrease in body weight. Adverse effects in the offspring occurred at maternal exposures at or above 0.6-times the recommended dose based on combined AUC for elafibranor and GFT1007. Stillbirths were observed in the 30 and 100 mg/kg/day groups (1.3 and 4.9-times the recommended dose, respectively, based on combined AUC for elafibranor and GFT1007). Aortic or iliac arterial thrombosis was found in decedent pups from females treated with 30 or 100 mg/kg/day. The surviving adult offspring showed no effects on learning and memory, reflex development, or reproductive capability.

8.2 Lactation

Risk Summary

There are no data available on the presence of elafibranor or its metabolites in human or animal milk, or on effects of the drug on the breastfed infant or the effects on milk production. Because of the potential for serious adverse reactions in the breastfed infant, advise patients not to breastfeed during treatment with IQIRVO, and for 3 weeks after the last dose.

8.3 Females and Males of Reproductive Potential

Based on animal data, IQIRVO may cause fetal harm when administered during pregnancy [see Use in Specific Populations (8.1)].

Pregnancy Testing

For females of reproductive potential, verify that the patient is not pregnant prior to initiating IQIRVO.

Contraception

Females

Advise females of reproductive potential to use effective contraception (non-hormonal) or add a barrier method of contraception when using hormonal contraceptives during treatment with IQIRVO and for 3 weeks after the last dose.

8.4 Pediatric Use

The safety and effectiveness of IQIRVO have not been established in pediatric patients.

8.5 Geriatric Use

Of the 108 IQIRVO-treated patients with PBC, 25 (23%) were 65 years of age and older, while 1 (1%) was 75 years of age and older. No overall differences in effectiveness of IQIRVO has been observed in patients 65 years of age and older compared to younger adult patients. In healthy elderly subjects (age range 75-80 years), mean systemic exposure (AUC) of elafibranor and the major active metabolite, GFT1007 was 23% and 52% higher, respectively, than those in healthy young subjects (age range 26 to 42 years).

No dosage adjustment for patients 65 years of age and older is necessary. However, because of limited clinical experience with IQIRVO in patients older than 75 years old, closer monitoring of adverse events in patients older than 75 years is recommended [see Clinical Pharmacology (12.3)].

8.6 Renal Impairment

The recommended dosage in patients with mild, moderate, or severe renal impairment is the same as in patients with normal kidney function [see Clinical Pharmacology (12.3)].

8.7 Hepatic Impairment

No dosage adjustment is recommended for patients with mild hepatic impairment (Child-Pugh A) [see Clinical Pharmacology (12.3)].

The safety and efficacy of IQIRVO in patients with decompensated cirrhosis have not been established. Use of IQIRVO is not recommended in patients who have or develop decompensated cirrhosis (e.g., ascites, variceal bleeding, hepatic encephalopathy). Monitor patients with cirrhosis for evidence of decompensation. Consider discontinuing IQIRVO if the patient progresses to moderate or severe hepatic impairment (Child-Pugh B or C).

11 DESCRIPTION

Elafibranor and its main active metabolite GFT1007 are peroxisome proliferator-activated receptor (PPAR) agonists. Elafibranor is practically insoluble in aqueous media at pH in the range 1.2 to 6.8. It is very slightly soluble at pH 7.5. It is soluble in dichloromethane, freely soluble in DMSO and sparingly soluble in 2-propanol and ethanol.

Its chemical formula is C22H24O4S, the molecular weight is 384.49 g/mol, the chemical name is 2-(2,6-Dimethyl-4-{3-[4-(methylsulfanyl)phenyl]-3-oxoprop-1-en-1-yl}phenoxy)-2-methylpropanoic acid and it has the following structural formula:

IQIRVO (elafibranor) tablets are supplied as 80 mg film-coated tablets for oral administration. Each tablet contains 80 mg elafibranor and the following inactive ingredients: colloidal silica dioxide, croscarmellose sodium, magnesium stearate, microcrystalline cellulose, and povidone. The film coating consists of: iron oxide red, iron oxide yellow, polyethylene glycol, polyvinyl alcohol, talc, and titanium dioxide.

12 CLINICAL PHARMACOLOGY

12.1 Mechanism of Action

Elafibranor and its main active metabolite GFT1007 are peroxisome proliferator-activated receptor (PPAR) agonists, both of which activate PPAR-alpha, PPAR-gamma, and PPAR-delta in vitro. However, the mechanism by which elafibranor exerts its therapeutic effects in patients with PBC is not well understood. Pharmacological activity that is potentially relevant to therapeutic effects includes inhibition of bile acid synthesis through activation of PPAR-alpha and PPAR-delta. The signaling pathway for PPAR-delta was reported to include Fibroblast Growth Factor 21 (FGF21)-dependent downregulation of CYP7A1, the key enzyme for the synthesis of bile acids from cholesterol.

An in vitro PPAR functional assay showed that both elafibranor and GFT1007 produced activation of PPAR-alpha (EC50 = 46 nM and 14 nM, respectively, and Emax = 56% and 61%, respectively, relative to reference agonists). The potency of elafibranor and GFT1007 for PPAR-alpha activation exceeded the respective potencies for PPAR-gamma and PPAR-delta activation by approximately 3- to 8-fold. Although the in vitro pharmacology studies detected PPAR-gamma activation by elafibranor and its metabolite GFT1007, toxicology studies in rats and monkeys (species with plasma metabolite profiles comparable to human) showed none of the adverse effects that are associated with PPAR-gamma activation.

12.2 Pharmacodynamics

In patients with PBC treated with 80 mg once daily of IQIRVO (Study 1), a greater reduction in mean alkaline phosphatase (ALP) from baseline was observed as early as 4 weeks after treatment compared to the placebo group and lower ALP was generally maintained through week 52 [see Clinical Studies (14)].

In another study, there was no apparent dose dependent increase in the reduction of ALP from baseline observed between 80 mg and 120 mg (1.5-times the recommended dose) once daily dosing in patients with PBC.

Cardiac Electrophysiology

At 3.75-times the recommended dose of 80 mg, IQIRVO did not cause clinically significant QTc interval prolongation.

12.3 Pharmacokinetics

Following once daily dosing, steady state of elafibranor was achieved by Day 14, while steady state of GFT1007 was achieved by Day 7. The pharmacokinetics (PK) of elafibranor and GFT1007 were time-independent after 16-day repeated administration. At steady state, mean AUC0-24h of elafibranor and GFT1007 increased 3.3-fold and 2.6-fold for a 2.5-fold dose increase from 40 mg to 100 mg and 2.9-fold and 2.2-fold, respectively from 120 mg to 300 mg. Mean AUC0-24 of GFT1007 was 3.2-fold higher than the elafibranor exposure in patients with PBC at steady state.

Table 5: Elafibranor and GFT1007 Systemic Exposures at Steady State in Patients with PBC Following 80 mg Once Daily
 | Cmax,ss (ng/mL) [Day 15 following repeated elafibranor 80 mg once daily administration in patients with PBC] Mean (SD) | AUC0-24 (ng ∙ h/mL) Mean (SD) | AUC ratio between Day 15/Day 1 Mean (min, max)
Elafibranor | 802 (443) | 3758 (1749) | 2.9 (0.86- to 13)
GFT1007 | 2058 (459) | 11985 (7149) | 1.3 (0.6- to 3)
Abbreviations: AUC = area under the concentration-versus-time curve; Cmax = maximum concentration; SS= Steady State

Absorption

Following once daily dosing of 80 mg in patients with PBC, median time to peak plasma concentrations (Tmax) of elafibranor and GFT1007 was 1.25 hours (range: 0.5-2 hours).

Effect of Food

When administered with a high-fat and high-calorie meal, Tmax was delayed by 30 minutes for elafibranor and by 1-hour for GFT1007 compared to in fasted conditions. Under fed condition, mean Cmax and AUC of elafibranor decreased by 50% and 15% respectively and mean Cmax of GFT1007 decreased by 30%, but the AUC was not affected compared to fasted conditions. The difference was not clinically meaningful.

Distribution

Plasma protein binding of both elafibranor and GFT1007 was approximately 99.7% (mainly to serum albumin). The mean apparent volume of distribution (Vd/F) of elafibranor in healthy subjects was 4731 L, following a single dose of elafibranor at 80 mg in fasted conditions.

Elimination

Following a single 80 mg dose under fasted conditions, median elimination half-life was 70.2 hours (range 37.1 to 92.2 hours) for elafibranor, and 15.4 hours (range 9.39 to 21.7 hours) for major active metabolite GFT1007. Elafibranor mean apparent total clearance (CL/F) was 50.0 L/h after a single 80 mg dose under fasted conditions.

Metabolism

Elafibranor is extensively metabolized to form a major active metabolite, GFT1007. The mean systemic exposure (AUC) to GFT1007 was 3.2-fold higher than that of elafibranor at steady state. Additional major inactive metabolite, an acyl glucuronide conjugate GFT3351 that consisted of four stereoisomers was formed.

In vitro studies showed that elafibranor was metabolized by cytosolic enzyme, 15-ketoprostaglandin 13-Δ reductase (PTGR1), to form GFT1007. Elafibranor was also metabolized by CYP2J2, and uridine diphosphate (UDP)-glucuronosyltransferase (UGT) isoforms, UGT1A3, UGT1A4, and UGT2B7. GFT1007 was further metabolized by CYP2C8 and UGT1A3 and UGT2B7.

Excretion

Following a single 120 mg oral dose (1.5-times the recommended dose) of ^14C-radiolabelled elafibranor in healthy subjects, approximately 77.1% of the dose was recovered in feces, primarily as elafibranor (56.7% of the administered dose) and its major metabolite GFT1007 (6.08% of the administered dose). Approximately 19.3% was recovered in urine, primarily as glucuronide conjugate GFT3351 (11.8% of the administered dose). A negligible amount of unchanged elafibranor or GFT1007 was detectable in the urine. Biliary excretion of elafibranor in humans was suggested by the excretion of 60% of orally administered elafibranor in the bile of rats.

Specific Populations

There was no evidence that sex and body mass index (BMI) (14.5 to 53.5 kg/m^2) or body weight (43 kg to 120 kg) had any clinically meaningful impact on PK of elafibranor and GFT1007.

Age

Following single dose 120 mg elafibranor administration (1.5-times the recommended dose), the AUCinf of elafibranor and GFT1007 was 23% and 51% higher, respectively in healthy elderly subjects (age range 75-80 years) than in healthy young subjects (age 26-42 years) [see Use in Specific Populations (8.5)].

Patients with Renal Impairment

Following a single dose of 120 mg elafibranor administration (1.5-times the recommended dose), the systemic exposure of elafibranor was 32% lower and GFT1007 was not significantly different between patients with normal renal function and patients with severe renal impairment (eGFR < 15 mL/min/1.73 m^2, Modification of Diet in Renal Disease (MDRD)) but not yet on dialysis. The unbound fraction of elafibranor was 21% lower and GFT1007 was not significantly different between patients with normal renal function and patients with severe renal impairment [see Use in Specific Populations (8.6)].

Patients with Hepatic Impairment

Following a single dose 120 mg elafibranor administration (1.5-times the recommended dose), no clinically significant differences in the pharmacokinetics of elafibranor or GFT1007 (mean change < 30%) were observed in patients with hepatic impairment (Child-Pugh A, B and C). However, the unbound fraction of elafibranor and GFT1007 was significantly increased by 2-fold and 2.6-fold, respectively, in patients with severe hepatic impairment (Child-Pugh C) [see Use in Specific Populations (8.7)].

Drug Interactions

Effect of IQIRVO on the Pharmacokinetics of Other Drugs

In vitro Studies:

Elafibranor, GFT1007 and GFT3351 did not inhibit CYP1A2, CYP2B6, CYP2C8, CYP2C9, CYP2C19, CYP2D6, and CYP3A4. No time dependent CYP inhibition is observed. Elafibranor and GFT1007 did not induce CYP1A2, CYP2B6, and CYP3A4. The CYP induction potential for GFT3351 was not assessed.

Elafibranor is not expected to inhibit UGT1A1, 1A3, 1A4, 1A6, 1A9, 2B7, 2B10, and 2B15 at the clinically relevant concentrations. GFT1007 is not expected to inhibit UGT1A1, 1A3, 1A4, 1A9, 2B7, 2B10, and 2B15 at the clinically relevant concentrations.

GFT1007 inhibited UGT1A6 but the clinical relevance of UGT1A6 inhibition is unknown.

Elafibranor is an inhibitor of bile salt export pump (BSEP) and breast cancer resistance protein (BCRP) and the clinical significance of BSEP and BCRP inhibition by elafibranor is unknown.

GFT3351 is an inhibitor of multidrug resistance associated protein 2 (MRP2) and MRP3 and the clinical significance of MRP2 and MRP3 inhibition by GFT3351 is unknown.

Elafibranor did not inhibit permeability-glycoprotein/multidrug resistance protein 1 (P-gp/MDR1), organic anion transporting polypeptides 1B1 (OATP1B1), organic cation transporter 1 (OCT1), OCT2, organic anion transporter 1 (OAT1), multidrug and toxin extrusion protein 1 (MATE1), MATE2-K and OAT3 and OATP1B3.

GFT1007 did not inhibit OAT3, OATP1B3, BSEP, P-gp/MDR1, BCRP, OATP1B1, OCT1, OCT2, OAT1, MATE1 and MATE2-K. GFT3351 did not inhibit BCRP, P-gp, OATP1B1, OATP1B3, OAT1, OAT2, OAT3, OCT1, OCT2, MATE1, MATE2-K, and BSEP.

Clinical Studies:

Warfarin (CYP2C9 Substrate):

No clinically significant differences in Cmax and AUC of S-warfarin and R-warfarin were observed when a single dose of warfarin 15 mg was administered with elafibranor 120 mg once daily at steady state compared to administered alone. No difference in international normalized ratio (INR) was observed.

Simvastatin (CYP3A4, OATP1B1 and OATP1B3 Substrates):

The active metabolite of simvastatin, simvastatin β-hydroxyacid Cmax decreased by 26% and AUCinf decreased by 32% following concomitant use of a single dose of simvastatin 20 mg and elafibranor 80 mg once daily at steady state. The change in simvastatin β-hydroxyacid exposure was not considered clinically meaningful. The results indicate that IQIRVO is a weak CYP3A4 inducer [see Drug Interaction (7.1)].

Atorvastatin (CYP3A, OATP1B1 and OATP1B3 Substrates):

Atorvastatin Cmax decreased by 28% and AUCinf decreased by 12% following concomitant use of a single dose of atorvastatin 40 mg and elafibranor 180 mg once daily at steady state. The change in atorvastatin exposure was not considered clinically meaningful.

Sitagliptin (dipeptidyl peptidase-IV (DPP-IV) Inhibitor):

In healthy subjects, no significant differences in plasma glucose and glucagon-like peptide-1 (GLP-1) were observed when elafibranor 120 mg was co-administered with sitagliptin 75 mg BID in comparison to administering sitagliptin alone. The relevance of the results to patients is unclear.

Effect of Other Drugs on the Pharmacokinetics of IQIRVO

In vitro Studies:

Elafibranor is a substrate of PTGR1 as well as CYP2J2 and UGT enzymes (e.g., UGT1A3, UGT1A4, and UGT2B7). GFT1007 is a substrate of CYP2C8 and UGT enzymes (e.g., UGT1A3 and UGT2B7).

Elafibranor is a substrate for MRP2 and BCRP. Potential impact of concomitant MRP2 or BCRP inhibitors was not studied in humans; thus, the clinical significance is unknown. GFT1007 is not a substrate for BCRP or MRP2. Neither elafibranor nor GFT1007 is a substrate of P-gp, OATP1B1, OATP1B3, OAT1, OAT3 and OCT2.

Clinical Study:

Indomethacin (PTGR1 Inhibitor):

No clinically significant differences in the pharmacokinetics (Cmax and AUC) of elafibranor and GFT1007 were observed when a single dose of elafibranor 120 mg was administered with indomethacin 75 mg after indomethacin was administered alone twice daily for 5 days.

13 NONCLINICAL TOXICOLOGY

13.1 Carcinogenesis, Mutagenesis, Impairment of Fertility

Carcinogenesis

In a 2-year study in CD-1 mice, oral administration of elafibranor produced hepatocellular tumors (adenoma or carcinoma) in both sexes at doses of 1, 3, 10, and 30 mg/kg/day (0.007 to 0.14 times the recommended dose in males and 0.003 to 0.16 times the recommended dose in females based on combined AUC for elafibranor and GFT1007).

In a 2-year study in Sprague-Dawley rats, oral administration of elafibranor produced hepatocellular tumors (adenoma or carcinoma) at 10 mg/kg/day and higher in males (0.36 times the recommended dose based on combined AUC for elafibranor and GFT1007) and at 30 mg/kg/day in females (2.1 times the recommended dose based on combined AUC for elafibranor and GFT1007). In males, elafibranor also produced pancreatic acinar cell adenoma and testicular Leydig cell adenoma at 30 mg/kg/day (2.1 times the recommended dose based on combined AUC for elafibranor and GFT1007).

The liver tumors in mice and rats may be attributed to the expected rodent-specific PPARα-related liver toxicity and its related consequences. Therefore, the relevance to humans is uncertain.

Mutagenesis

Elafibranor was negative in the in vitro bacterial reverse mutation (Ames) assay, the in vivo rat micronucleus assay, and the in vivo rat comet assay. Elafibranor was mutagenic in L5178Y tk+/- mouse lymphoma cells in the absence or presence of metabolic activation and it induced the formation of micronuclei in this cell line in the presence of metabolic activation.

The metabolites GFT1007 and racemic GFT3351 were both negative in the in vitro bacterial reverse mutation (Ames) assay. GFT1007 tested negative in the in vitro micronucleus assay in L5178Y tk+/- mouse lymphoma cells, and GFT3351 tested negative in the in vitro micronucleus assay in human lymphocytes.

The overall data and weight-of-evidence from the comprehensive battery of in vivo and in vitro genotoxicity assays conducted for elafibranor, its principal active metabolite GFT1007, and the acyl glucuronide metabolite racemic GFT3351 indicate that the parent drug and its tested metabolites are unlikely to have genotoxic potential.

Impairment of Fertility

Elafibranor produced no adverse effects on rat fertility or early embryonic development at oral doses up to 100 mg/kg/day (5.9 times the recommended dose in females and 7.4 times the recommended dose in males based on combined AUC for elafibranor and GFT1007).

14 CLINICAL STUDIES

The efficacy of IQIRVO was evaluated in Study 1 (NCT04526665), a multi-center, randomized, double-blind, placebo-controlled study. The study included 161 adults with PBC with an inadequate response or intolerance to UDCA. Patients were randomized to receive IQIRVO 80 mg (n=108) or placebo (n=53) once daily for at least 52 weeks. When applicable, patients continued their pre-study dose of UDCA throughout the study. Patients were included in the study if their ALP was greater than or equal to 1.67-times the ULN and TB was less than or equal to 2-times the ULN. Patients were excluded if they had other liver disease or in case of decompensated cirrhosis.

The mean age of patients in Study 1 was 57 (Range: 36, 76) years, and the mean weight was 70.8 (Range: 43, 134) kg. The study population was predominately female (96%) and White (91%). The baseline mean ALP concentration was 321.9 (Range: 151, 1398) U/L, and 39% of patients had a baseline ALP concentration greater than 3-times the ULN.

The mean baseline TB concentration was 0.56 (Range: 0.15, 1.76) mg/dL, and 96% of patients had a baseline TB concentration less than or equal to ULN. The baseline mean concentration of ALT was 50 (Range: 11 to 188) U/L and mean baseline concentration for AST was 46 (Range: 14 to 203) U/L.

Most patients (95%) received study treatment (IQIRVO or placebo) in combination with UDCA. There were 6 (6%) in the IQIRVO-treated patients and 2 (4%) in the placebo-treated patients who were unable to tolerate UDCA and received IQIRVO as monotherapy. At baseline, 12 (11%) of the IQIRVO-treated patients and 8 (15%) of the placebo-treated patients met at least one of the following criteria: serum albumin < 3.5g/dL, INR >1.3, TB > 1-time ULN, Fibroscan >16.9 kPa, or historical biopsy suggestive of cirrhosis.

The primary endpoint was biochemical response at Week 52, where biochemical response was defined as achieving ALP less than 1.67-times ULN, TB less than or equal to ULN, and ALP decrease greater than or equal to 15% from baseline. The ULN for ALP was defined as 129 U/L for males and 104 U/L for females. The ULN for TB was defined as 1.20 mg/dL. ALP normalization (i.e., ALP less than or equal to ULN) at Week 52 was a key secondary endpoint.

Table 6 presents results at Week 52 for the percentage of patients who achieved biochemical response, achieved each component of biochemical response, and achieved ALP normalization. IQIRVO demonstrated greater improvement on biochemical response and ALP normalization at Week 52 compared to placebo. Overall, 96% of patients had a baseline TB concentration less than or equal to ULN. Therefore, improvement in ALP was the main contributor to the biochemical response rate results at Week 52.

Table 6: Percentage of Adult Patients with PBC Achieving Biochemical Response and ALP Normalization at Week 52 in Study 1 [Patients who prematurely stopped the study treatment or used rescue therapy for PBC prior to the Week 52 assessment were considered non-responders. For two other patients with missing data at Week 52, the closest non-missing assessment from the double-blind treatment period was used.]
 | IQIRVO 80mg Once Daily (N=108) | Placebo (N=53) | Treatment Difference, % (95% CI) [For biochemical response and its components: calculated using the Newcombe method stratified by (1) ALP > 3-times ULN or TB > ULN (Yes/No) and (2) 14-day baseline average PBC Worst Itch Numeric Rating Scale score ≥ 4 (Yes/No). For ALP normalization: calculated using unstratified Newcombe method.]
Biochemical response rate, n (%) [Biochemical response is defined as ALP <1.67-times ULN and TB ≤ULN and ALP decrease from baseline ≥ 15% at Week 52. The p-value from the exact Cochran–Mantel–Haenszel (CMH) test was <0.0001.] | 55 (51) | 2 (4) | 47 (32, 57)
Components of biochemical response
ALP less than 1.67-times ULN, n (%) | 56 (52) | 5 (9) | 42 (27, 53)
Decrease in ALP of at least 15%, n (%) | 81 (75) | 9 (17) | 58 (43, 69)
TB less than or equal to ULN, n (%) [The mean baseline total bilirubin was 0.56 mg/dL, and was less than or equal to the ULN in 96% of the enrolled patients.] | 92 (85) | 44 (83) | 2 (-9, 16)
ALP normalization, n (%) [Normalization of ALP at Week 52 is defined as ALP ≤1-time ULN. The p-value from the exact CMH test was 0.0019.] | 16 (15) | 0 (0) | 15 (6, 23)

Figure 1 depicts the mean (95% confidence interval) ALP levels over 52 weeks. There was a trend of lower ALP in the IQIRVO group compared to the placebo group starting by Week 4 through Week 52.

Figure 1: Mean ALP (+/- 95% Confidence Interval) in Adult Patients with PBC Over 52 Weeks in Study 1

Missing data and data following study treatment discontinuation was imputed by multiple imputation.

16 HOW SUPPLIED/STORAGE AND HANDLING

How Supplied

IQIRVO (elafibranor) tablets are available as 80 mg, round, orange, film-coated tablets, debossed with 'ELA 80' on one side and plain on the other side.

IQIRVO is supplied in a child-resistant 30 count bottle (NDC 15054-0080-1).

Storage and Handling

Store at room temperature 15°C to 30°C (59°F to 86° F).

Store in the original package (bottle and carton) to protect from moisture and light.

17 PATIENT COUNSELING INFORMATION

Advise the patient to read the FDA-approved patient labeling (Medication Guide).

Myalgia, Myopathy, and Rhabdomyolysis

Advise patients that IQIRVO may cause rhabdomyolysis. Inform patients to report immediately to their healthcare provider any unexplained muscle symptoms such as pain, soreness, or weakness [see Warnings and Precautions (5.1)].

Fractures

Inform patients or their caregiver(s) that IQIRVO may increase the risk of bone fractures. Advise patients to call their healthcare provider to report any fractures [see Warnings and Precautions (5.2)].

Adverse Effects on Fetal and Newborn Development

Advise pregnant women and females of reproductive potential of the potential risk to the fetus and to inform their healthcare providers of a known, suspected, or planned pregnancy during treatment with IQIRVO. Inform patients to report their pregnancy to Ipsen Biopharmaceuticals, Inc. at (1-855-463-5217). Advise females of reproductive potential to use effective contraception during treatment and for 3 weeks after the last dose of IQIRVO [see Warning and Precautions (5.3), Use in Specific Population (8.1, 8.3)].

Lactation

Advise women not to breastfeed during treatment with IQIRVO and for 3 weeks after the last dose [see Use in Specific Populations (8.2)].

Drug-Induced Liver Injury

Inform patients of the risk of IQIRVO-induced liver injury. Instruct patients to report any signs or symptoms of liver injury (e.g., loss of appetite, nausea, increased fatigue, lower extremity edema, abdominal swelling, or jaundice/icterus) to their healthcare provider [see Warnings and Precautions (5.4)].

Hypersensitivity Reactions

Advise patients to contact their healthcare provider or go to the emergency department if hypersensitivity reactions, such as rash, occur [see Warnings and Precautions (5.5)].

Biliary Obstruction

Instruct patients to immediately report any signs or symptoms of biliary obstruction (e.g., right upper quadrant pain, jaundice) to their healthcare provider so that IQIRVO treatment can be interrupted while the patient is being evaluated [see Warnings and Precautions (5.6)].

Manufactured for: Ipsen Biopharmaceuticals, Inc., One Main Street, 7th Floor, Cambridge, MA, 02142, USA

MEDICATION GUIDE
IQIRVO® (eye-ker-vo)
(elafibranor) tablets

What is IQIRVO?
IQIRVO is a prescription medicine used to treat primary biliary cholangitis (PBC) in combination with ursodeoxycholic acid (UDCA) in adults who have not responded well to UDCA, or used alone in patients unable to tolerate UDCA.
IQIRVO is not recommended for use in people who have symptoms or signs of advanced liver disease (decompensated cirrhosis) including confusion; having fluid in the stomach-area (abdomen); black, tarry, or bloody stools; coughing up or vomiting blood, or having vomit that looks like "coffee grounds."
It is not known if taking IQIRVO will improve your chance of survival or prevent liver decompensation.
It is not known if IQIRVO is safe and effective in children under 18 years of age.

Before taking IQIRVO, tell your healthcare provider about all of your medical conditions, including if you:

- have advanced liver disease.
- are pregnant or plan to become pregnant. IQIRVO can harm your unborn baby. You should not become pregnant during treatment with IQIRVO.
  Pregnancy Safety Study. If you become pregnant while receiving IQIRVO, tell your healthcare provider right away. There is a pregnancy safety study for women who become pregnant while taking IQIRVO. Talk to your healthcare provider about providing information to the IQIRVO pregnancy safety study. The purpose of this study is to collect information about your health and your baby's health. You or your healthcare provider can report your pregnancy by calling 1-855-463-5217 or visiting https://www.ipsen.com/contact-us/.
- are breastfeeding or plan to breastfeed. It is not known if IQIRVO passes into your breast milk. Do not breastfeed while taking IQIRVO and for 3 weeks after the last dose of IQIRVO. Talk with your healthcare provider about the best way to feed your baby if you take IQIRVO.

Your healthcare provider should check for muscle pain or weakness before your start taking IQIRVO. Tell your health care provider right away If you have new and/or severe muscle pain or muscle weakness.
Females who can become pregnant:

- You should use effective birth control during treatment and for 3 weeks after the last dose of IQIRVO. Talk to your healthcare provider about birth control methods that may be right for you.
- Tell your healthcare provider right away if you become pregnant or think you may be pregnant.

Tell your healthcare provider about all of the medicines you take, including prescription and over-the-counter medicines, vitamins, and herbal supplements. IQIRVO can affect the way certain medicines work. Certain medicine may affect the way IQIRVO works.

How should I take IQIRVO?

- Take IQIRVO exactly as your healthcare provider tells you to.
- Take IQIRVO with or without food.
- If you take a bile acid binding resin, take IQIRVO at least 4 hours before or 4 hours after you take your bile acid binding resin. If this is not possible, space the time between taking IQIRVO and your bile acid binding resin as far apart as possible.
- If you take too much IQIRVO, call your healthcare provider or get emergency medical help right away.

What are the possible side effects of IQIRVO?
IQIRVO can cause serious side effects including:

- Muscle problems (myalgia, myopathy, rhabdomyolysis). IQIRVO can cause muscle pain that can be severe. Treatment with IQIRVO may cause muscle pain or worsen existing pain and can increase the level of an enzyme in your blood called creatine phosphokinase (CPK); both can be a sign of muscle damage. Your healthcare provider should test for muscle weakness or pain before and during treatment. If there is new onset or worsening of muscle pain then your healthcare provider may examine you and perform a blood test to check your levels of creatine phosphokinase (CPK). Stop taking IQIRVO and call your healthcare provider right away if you have any of the following signs or symptoms:

- severe muscle pain
- unexplained soreness

- unexplained muscle weakness
- dark, reddish urine

- Bone fractures. Taking IQIRVO may increase your risk of bone fractures. Tell your healthcare provider about any bone fractures, or if you develop pain, or have changes in your ability to move around.
- Liver problems. IQIRVO may cause abnormal liver blood test results. Your healthcare provider should do tests before starting and during treatment with IQIRVO to check your liver function.
  Tell your healthcare provider right away if you have any of the following signs or symptoms of worsening liver problems, during treatment with IQIRVO:

- swelling of your stomach-area (abdomen) from a build-up of fluid
- yellowing of your skin or the whites of your eyes
- black, tarry, or bloody stools
- coughing up or vomiting blood, or your vomit looks like "coffee grounds"

- mental changes such as confusion, being sleepier than usual or harder to wake up, slurred speech, mood swings, or changes in personality

Tell your healthcare provider right away if you have any of the following symptoms during treatment with IQIRVO and they are severe or do not go away:

- stomach-area (abdomen) pain
- nausea, vomiting, diarrhea
- loss of appetite or weight loss
- new or worsening fatigue

- weakness
- fever and chills
- light-headedness
- less frequent urination

- Allergic reactions. Some people taking IQIRVO have had allergic reactions. The reactions happened 2 to 30 days after taking IQIRVO. Allergic reaction symptoms may include:

- rash
- trouble breathing

- itching
- swelling of your face, lips, tongue, or throat.

If you have any of these symptoms stop taking IQIRVO and call your healthcare provider right away or go to the nearest hospital emergency room.

- Blockage of the bile duct. Taking IQIRVO may increase your risk of gallstone development. Call your healthcare provider right away if you develop any signs or symptoms of gallstones, including pain in upper right stomach area or yellowing of the skin.

The most common side effects of IQIRVO include:

- weight gain
- diarrhea
- nausea and vomiting
- joint pain
- stomach pain

- constipation
- muscle problems
- bone fractures
- gastroesophageal reflux disease (GERD)

- dry mouth
- weight loss
- rash

Your healthcare provider may tell you to stop taking IQIRVO temporarily or permanently if there are changes to either your liver tests or the level of an enzyme in your blood related to muscle activity called creatine phosphokinase (CPK).
Call your doctor for medical advice about side effects. You may report side effects to FDA at 1-800-FDA-1088.

How should I store IQIRVO?

- Store IQIRVO at room temperature between 15°C to 30°C (59°F to 86°F).
- Store in the original package (bottle and carton) to protect from moisture and light.

Keep IQIRVO and all medicines out of the reach of children.

General information about the safe and effective use of IQIRVO.
Medicines are sometimes prescribed for purposes other than those listed in a Medication Guide. Do not use IQIRVO for a condition for which it was not prescribed. Do not give IQIRVO to other people even if they have the same symptoms that you have. It may harm them. You can ask your pharmacist or healthcare provider for information about IQIRVO that is written for health professionals.

What are the ingredients in IQIRVO?
Active ingredient: Elafibranor
Inactive ingredients: colloidal silica dioxide, croscarmellose sodium, magnesium stearate, microcrystalline cellulose, and povidone. The film coating consists of: iron oxide red, iron oxide yellow, polyethylene glycol, polyvinyl alcohol, talc, and titanium dioxide.
Manufactured for: Ipsen Biopharmaceuticals, Inc., One Main Street, 7th Floor, Cambridge, MA, 02142, USA
For more information, 1-855-463-5127
IQIRVO is a registered trademark of Genfit SA
© 2024 Ipsen Biopharmaceuticals, Inc. All rights reserved

This Medication Guide has been approved by the U.S. Food and Drug Administration

Approved: 06/2024

PRINCIPAL DISPLAY PANEL - 80 mg Tablet Bottle Carton

Rx only
NDC 15054-0080-1

IQIRVO®
(elafibranor)
tablets

80 mg

For Oral Use

30
tablets